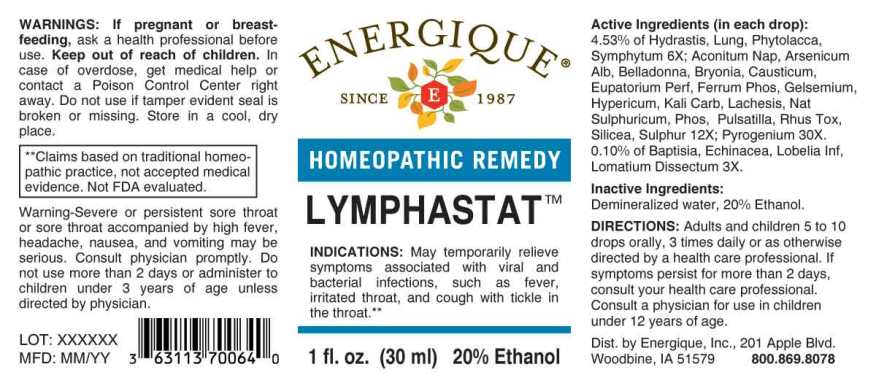 DRUG LABEL: Lymphastat
NDC: 44911-0615 | Form: LIQUID
Manufacturer: Energique, Inc.
Category: homeopathic | Type: HUMAN PRESCRIPTION DRUG LABEL
Date: 20241028

ACTIVE INGREDIENTS: BAPTISIA TINCTORIA ROOT 3 [hp_X]/1 mL; ECHINACEA ANGUSTIFOLIA WHOLE 3 [hp_X]/1 mL; LOBELIA INFLATA WHOLE 3 [hp_X]/1 mL; LOMATIUM DISSECTUM ROOT 3 [hp_X]/1 mL; GOLDENSEAL 6 [hp_X]/1 mL; SUS SCROFA LUNG 6 [hp_X]/1 mL; PHYTOLACCA AMERICANA ROOT 6 [hp_X]/1 mL; COMFREY ROOT 6 [hp_X]/1 mL; ACONITUM NAPELLUS WHOLE 12 [hp_X]/1 mL; ARSENIC TRIOXIDE 12 [hp_X]/1 mL; ATROPA BELLADONNA 12 [hp_X]/1 mL; BRYONIA ALBA ROOT 12 [hp_X]/1 mL; CAUSTICUM 12 [hp_X]/1 mL; EUPATORIUM PERFOLIATUM FLOWERING TOP 12 [hp_X]/1 mL; FERROSOFERRIC PHOSPHATE 12 [hp_X]/1 mL; GELSEMIUM SEMPERVIRENS ROOT 12 [hp_X]/1 mL; HYPERICUM PERFORATUM WHOLE 12 [hp_X]/1 mL; POTASSIUM CARBONATE 12 [hp_X]/1 mL; LACHESIS MUTA VENOM 12 [hp_X]/1 mL; SODIUM SULFATE 12 [hp_X]/1 mL; PHOSPHORUS 12 [hp_X]/1 mL; PULSATILLA PRATENSIS WHOLE 12 [hp_X]/1 mL; TOXICODENDRON PUBESCENS LEAF 12 [hp_X]/1 mL; SILICON DIOXIDE 12 [hp_X]/1 mL; SULFUR 12 [hp_X]/1 mL; RANCID BEEF 30 [hp_X]/1 mL
INACTIVE INGREDIENTS: WATER; ALCOHOL

Drug Facts:

ACTIVE INGREDIENTS:

(in each drop): 4.53% of Hydrastis Canadensis 6X, Lung (Suis) 6X, Phytolacca Decandra 6X, Symphytum Officinale 6X; Aconitum Napellus 12X, Arsenicum Album 12X, Belladonna 12X, Bryonia 12X, Causticum 12X, Eupatorium Perfoliatum 12X, Ferrum Phosphoricum 12X, Gelsemium Sempervirens 12X, Hypericum Perforatum 12X, Kali Carbonicum 12X, Lachesis Mutus 12X, Natrum Sulphuricum 12X, Phosphorus 12X, Pulsatilla (Pratensis) 12X, Rhus Tox 12X, Silicea 12X, Sulphur 12X; Pyrogenium 30X. 0.10% of Baptisia Tinctoria 3X, Echinacea (Angustifolia) 3X, Lobelia Inflata 3X, Lomatium Dissectum 3X.

INDICATIONS:

May temporarily relieve symptoms associated with viral and bacterial infections, such as fever, irritated throat, and cough with tickle in the throat.**

**Claims based on traditional homeopathic practice, not accepted medical evidence. Not FDA evaluated.

WARNINGS:

If pregnant or breast-feeding, ask a health professional before use.

Keep out of reach of children. In case of overdose, get medical help or contact a Poison Control Center right away.

Do not use if tamper evident seal is broken or missing.

Store in a cool, dry place.

Keep out of reach of children. In case of overdose, get medical help or contact a Poison Control Center right away.

DIRECTIONS:

Adults and children 5 to 10 drops orally, 3 times daily or as otherwise directed by a health care professional. If symptoms persist for more than 2 days, consult your health care professional. Consult a physician for use in children under 12 years of age.

INDICATIONS:

May temporarily relieve symptoms associated with viral and bacterial infections, such as fever, irritated throat, and cough with tickle in the throat.**

**Claims based on traditional homeopathic practice, not accepted medical evidence. Not FDA evaluated.

INACTIVE INGREDIENTS:

Demineralized water, 20% Ethanol.

QUESTIONS:

Dist. by Energique, Inc.
201 Apple Blvd
Woodbine, IA 51579 800.869.8078

PACKAGE LABEL DISPLAY:

ENERGIQUE

SINCE 1987

HOMEOPATHIC REMEDY

LYMPHASTAT

1 fl. oz. (30 ml)